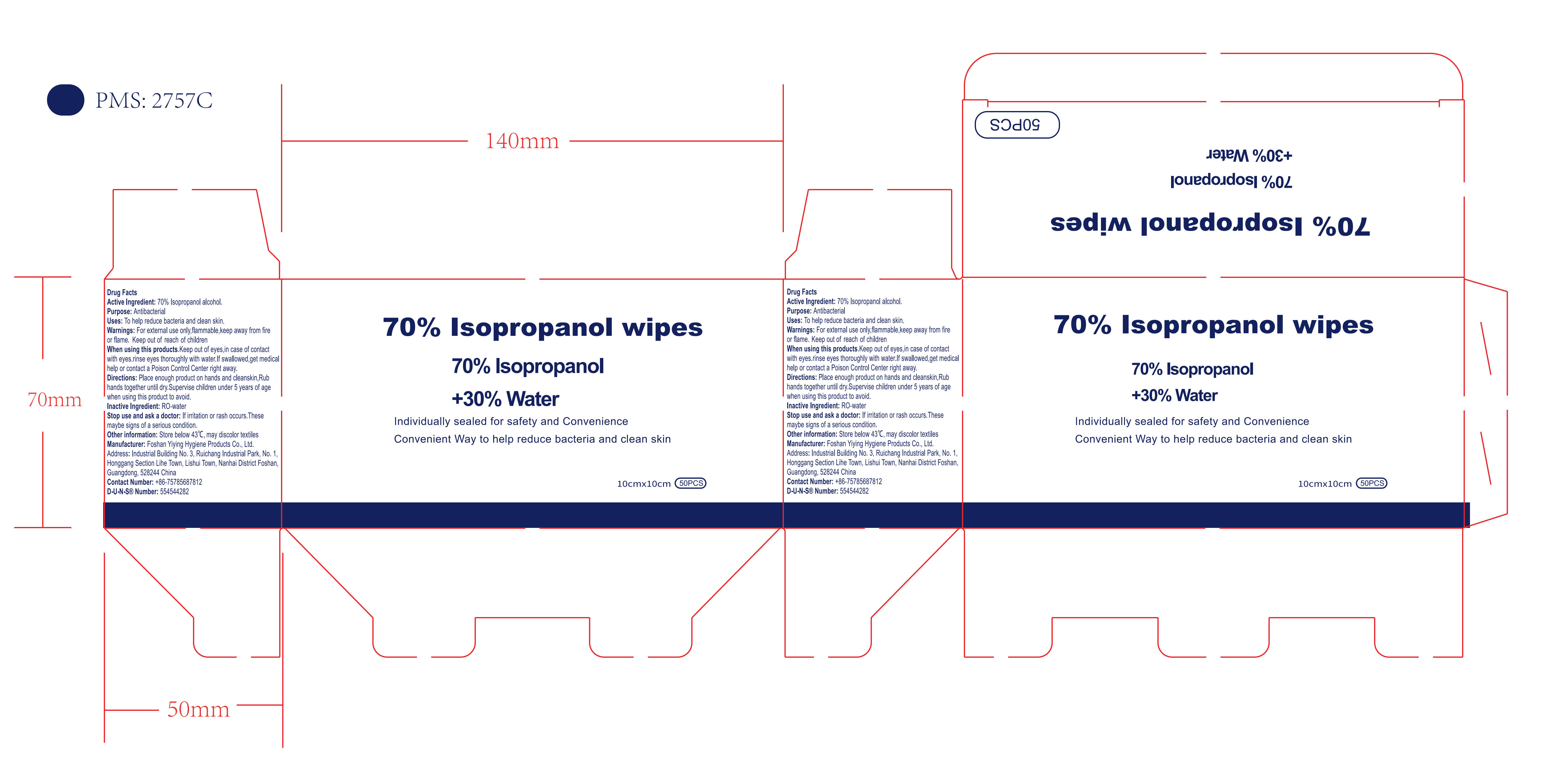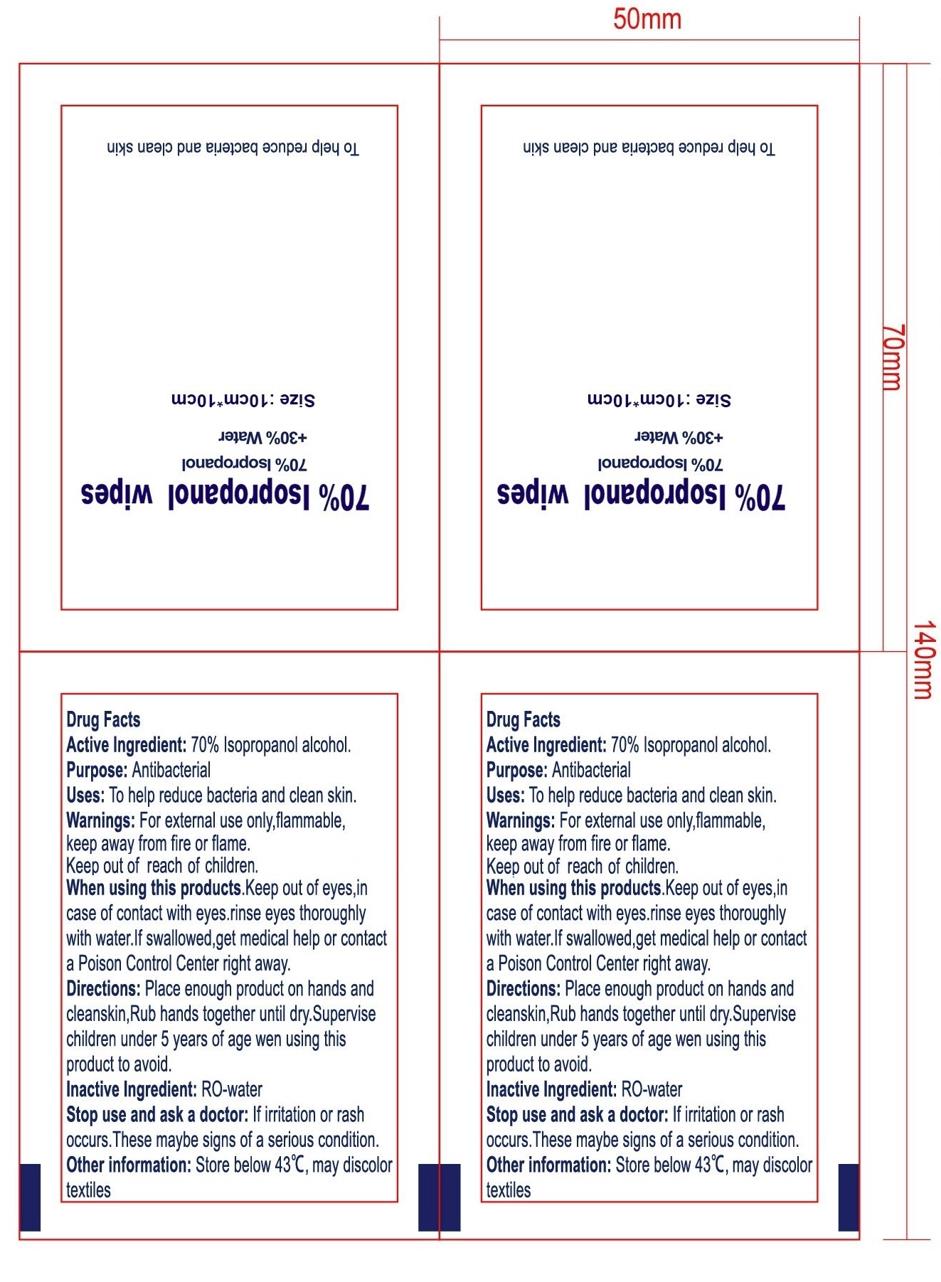 DRUG LABEL: 70% Isopropanol wipes
NDC: 80139-201 | Form: CLOTH
Manufacturer: Foshan Yiying Hygiene Products Co., Ltd.
Category: otc | Type: HUMAN OTC DRUG LABEL
Date: 20220118

ACTIVE INGREDIENTS: ISOPROPYL ALCOHOL 1.07 mL/1 1
INACTIVE INGREDIENTS: WATER

70% Isopropanol Wipes

Active Ingredient(s)

Isopropanol Alcohol, 70% w/w, 1.07 mL/pcs. Purpose: Antibacterial

Purpose

Antibacterial

Use

To help reduce bacteria and clean skin.

Warnings

For external use only, flammable, keep away from fire or flame.

Do not use on eyes, open skin wounds.

When using this product

Keep out of eyes, in case of contact with eyes, rinse eyes thoroughly with water. If swallowed, get medical help or contact a Poison Control Center right away.

Stop use and ask a doctor

If irritation or rash occurs. These may be signs of a serious condition.

Keep out of reach of children. If swallowed, get medical help or contact a Poison Control Center right away.

Directions

Place enough product on hands and clean skin. Rub hands together until dry. Supervise children under 5 years of age when using this product to avoid.

Other information

Store below 43℃, may discolor textiles

Inactive Ingredient(s)

RO-water